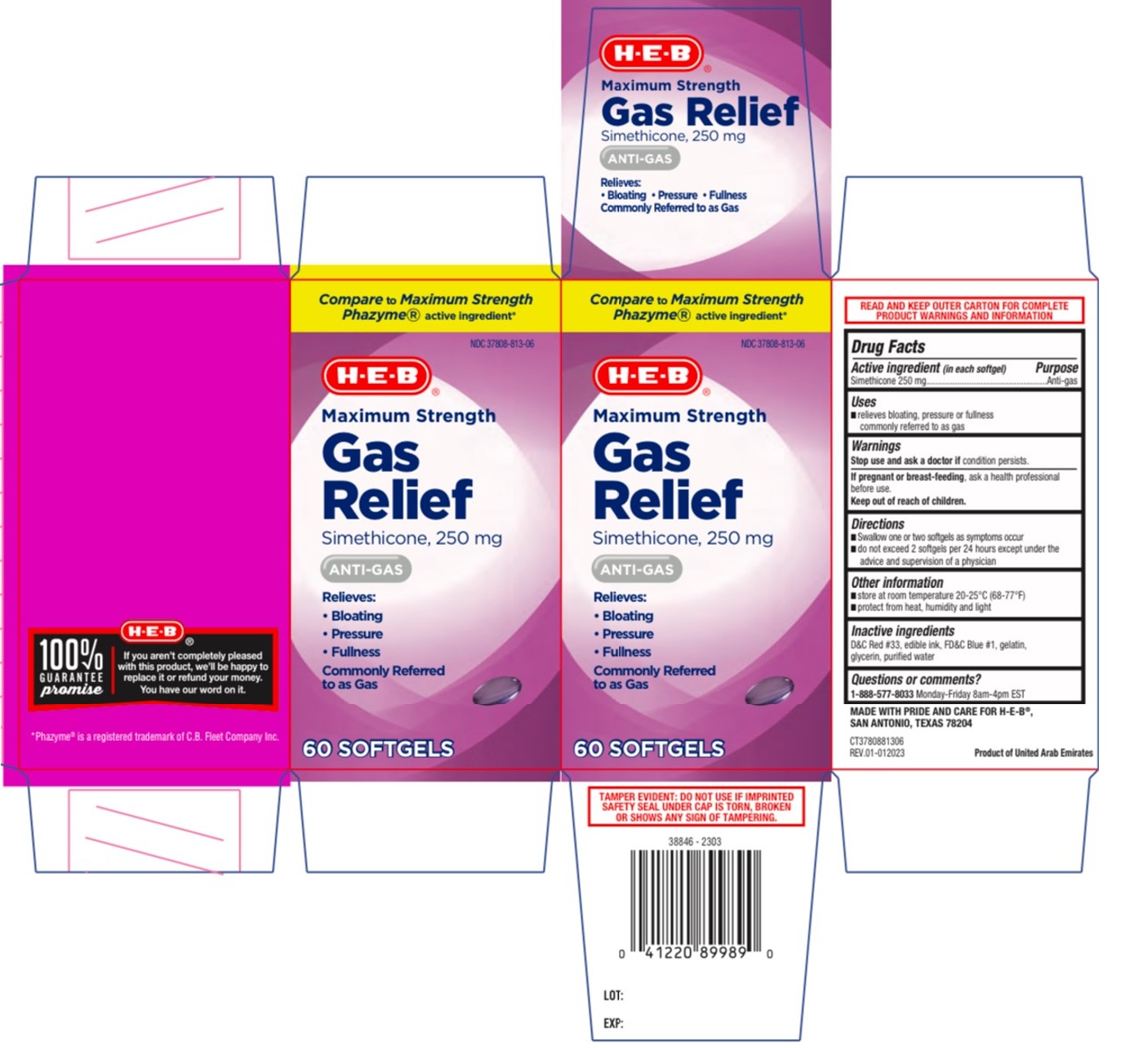 DRUG LABEL: Maximum Strength Gas Relief Softgel-60ct
NDC: 37808-813 | Form: CAPSULE, LIQUID FILLED
Manufacturer: HEB
Category: otc | Type: HUMAN OTC DRUG LABEL
Date: 20241216

ACTIVE INGREDIENTS: DIMETHICONE, UNSPECIFIED 250 mg/1 1
INACTIVE INGREDIENTS: D&C RED NO. 33; FD&C BLUE NO. 1; GELATIN, UNSPECIFIED; GLYCERIN; WATER

H-E-B® Maximum Strength Gas Relief

Active ingredient (in each softgel)

Simethicone 250 mg

Purpose

Anti-gas

Uses

- relieves bloating, pressure or fullness commonly referred to as gas

Warnings

Stop use and ask a doctor if condition persists.

If pregnant or breast-feeding, ask a health professional before use.

Keep out of reach of children.

Directions

- Swallow one or two softgels as symptoms occur
- do not exceed 2 softgels per 24 hours except under the advice and supervision of a physician

Other information

- store at room temperature 20-25°C (68-77°F)
- protect from heat, humidity and light

Inactive ingredients

D&C Red #33, edible ink, FD&C Blue #1, gelatin, glycerin, purified water

Questions or comments?

1-888-577-8033 Monday-Friday 8am-4pm EST

Compare to Maximum Strength Phazyme® active ingredient*

Relieves:
• Bloating
• Pressure
• Fullness
Commonly Referred to as Gas

TAMPER EVIDENT: DO NOT USE IF IMPRINTED SAFETY SEAL UNDER CAP IS TORN, BROKEN OR SHOWS ANY SIGN OF TAMPERING.

READ AND KEEP OUTER CARTON FOR COMPLETE PRODUCT WARNINGS AND INFORMATION

MADE WITH PRIDE AND CARE FOR H-E-B®,
SAN ANTONIO, TEXAS 78204

Product of United Arab Emirates

100% GUARANTEE promise

If you aren't completely pleased with this product, we'll be happy to replace it or refund your money. You have our word on it.

*Phazyme® is a registered trademark of C.B. Fleet Company Inc.